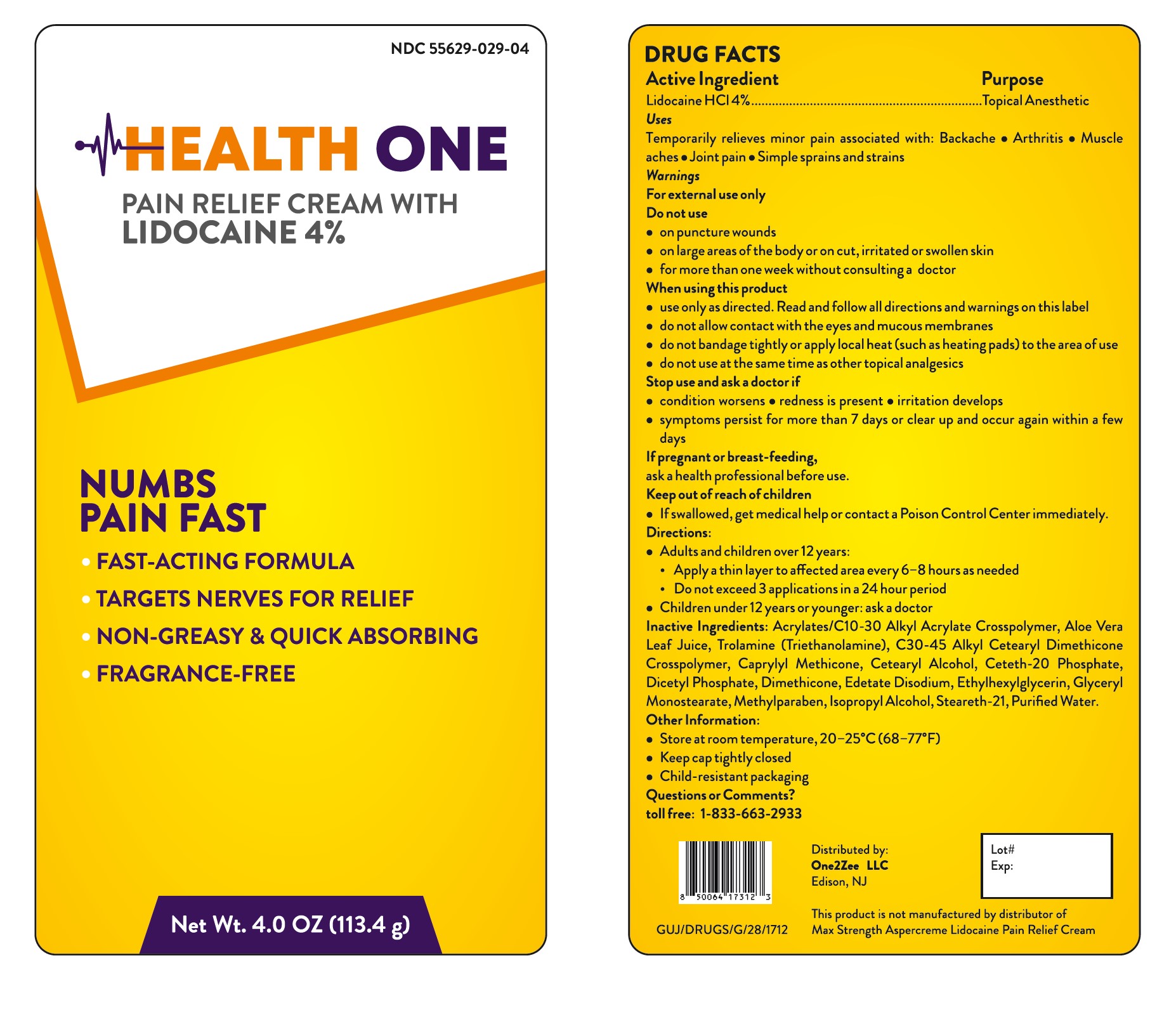 DRUG LABEL: Health One Pain Relief Cream with Lidocaine 4%
NDC: 55629-029 | Form: CREAM
Manufacturer: ONE2ZEE LIMITED LIABILITY COMPANY
Category: otc | Type: HUMAN OTC DRUG LABEL
Date: 20251203

ACTIVE INGREDIENTS: LIDOCAINE 0.4 g/1 g
INACTIVE INGREDIENTS: ACRYLATES/C10-30 ALKYL ACRYLATE CROSSPOLYMER (60000 MPA.S); ALOE VERA LEAF JUICE; TROLAMINE; C30-45 ALKYL CETEARYL DIMETHICONE CROSSPOLYMER; CETEARYL ALCOHOL; DIMETHOCAINE; EDETATE DISODIUM; ETHYLHEXYLGLYCERIN; GLYCERYL MONOSTEARATE; METHYLPARABEN; ISOPROPYL ALCOHOL; STEARETH-21; WATER

Pain Relief Cream with Lidocaine 4%

Drug Facts

Active Ingredient

Lidocaine HCI 4%

Purpose

Topical anesthetic

Uses

temporarily relieves minor pain

Warnings

For external use only

Do not use

- on puncture wounds
- on large areas of the body or on cut, irritated or swollen skin
- for more than one week without consulting a doctor

When using this product

- use only as directed. Read and follow all directions and warnings on this carton.
- do not allow contact with the eyes and mucous membranes
- do not bandage or apply local heat (such as heating pads) to the area of use
- do not use at the same time as other topical analgesics

Stop use and ask a doctor if

- condition worsens
- redness is present
- irritation develops
- symptoms persist for more than 7 days or clear up and occur again within a few days

If pregnant or breast-feeding,

ask a health professional before use.

Keep out of reach of children and pets.

If swallowed, get medical help or contact a Poison Control Center right away.

Directions

adults and children over 12 years:

- apply a thin layer to affected area every 6 to 8 hours, not to exceed 3 applications in a 24 hour period

children 12 years and younger: ask a doctor

Inactive ingredients

acrylates/C10-30 alkyl acrylate crosspolymer,, Aloe Vera Leaf Juice, Trolamine, C30-45 alkyl cetearyl dimethicone crosspolymer, Cetearyl Alcohol, Dimethocane, Edetate Disodium, Ethylhexylglycerin, Glyceryl Monostearate, Methylparaben, Isopropyl Alcohol, Steareth-21, Purified Water